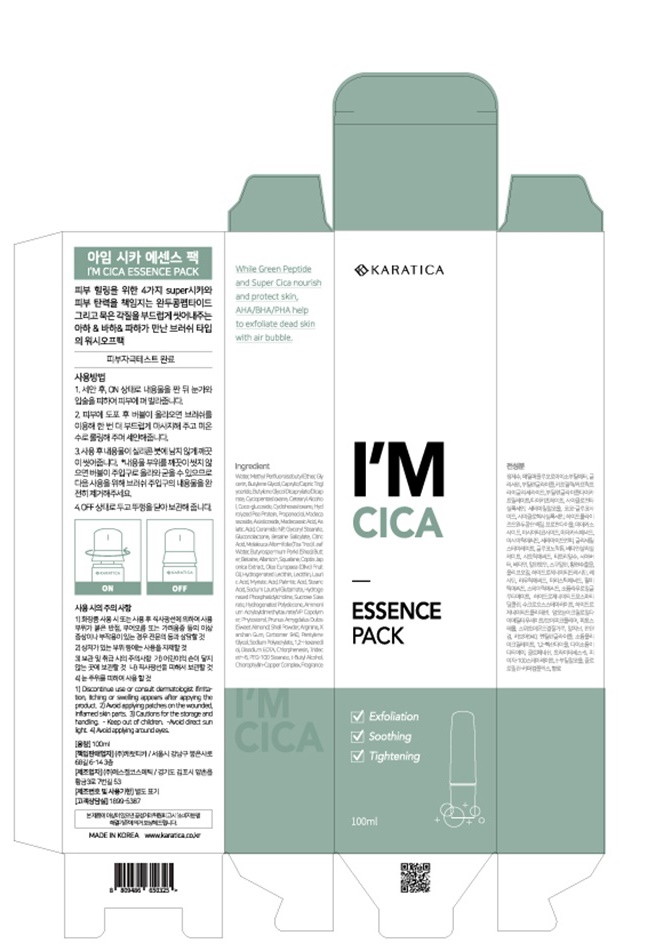 DRUG LABEL: KARATICA IM CICA ESSENCE PACK
NDC: 70514-0013 | Form: LIQUID
Manufacturer: Karatica Co., Ltd
Category: otc | Type: HUMAN OTC DRUG LABEL
Date: 20190816

ACTIVE INGREDIENTS: ASIATICOSIDE 0.01 g/100 mL; MADECASSOSIDE 0.01 g/100 mL; MADECASSIC ACID 0.01 g/100 mL; ASIATIC ACID 0.01 g/100 mL
INACTIVE INGREDIENTS: WATER

ACTIVE INGREDIENT

Madecassoside, Asiaticoside, Madecassic Acid, Asiatic Acid

INACTIVE INGREDIENT

Water
MethylPerfluoroisobutylEther
Glycerin
ButyleneGlycol
Caprylic/CapricTriglyceride
ButyleneGlycolDicaprylate/Dicaprate
Cyclopentasiloxane
CetearylAlcohol
Coco-glucoside
Cyclohexasiloxane
GlycerylStearate
PEG-100 Stearate
PalmiticAcid
AmmoniumAcryloyldimethyltaurate/VP Copolymer
StearicAcid
SodiumLauroylGlutamate
HydrogenatedLecithin
CoptisJaponicaExtract
Propanediol
HydrolyzedPeaProtein
Prunus Amygdalus Dulcis (Sweet Almond) Shell Powder
Carbomer 940
Arginine
Betaine
ButyrospermumParkii (Shea) Butter
Ceramide NP
Melaleuca Alternifolia (Tea Tree) Leaf Water
Chlorophyllin-Copper Complex
CitricAcid
BetaineSalicylate
Gluconolactone
XanthanGum
HydrogenatedPolydecene
LauricAcid
MyristicAcid
SucroseStearate
Phytosterol
HydrogenatedPhosphatidylcholine
Lecithin
Olea Europaea (Olive) Fruit Oil
Squalane
SodiumPolyacrylate
Allantoin
1,2-Hexanediol
PentyleneGlycol
Chlorphenesin
Disodium EDTA
Fragrance
t-ButylAlcohol
Trideceth-6

PURPOSE

Removal of sebum and waste

keep out or reach of the children

INDICATIONS AND USAGE

1.Turn on the brush and press the tube.
2.Gently apply on face avoiding eyes and lips and wait for bubbles.
3.When bubble forms, softly massage face with brush. Then wash off with warm water.
4.Make sure to turn off the brush and cleanse the brush after each use.

WARNINGS

1) Discontinue use or consult dermatologist if irritation, itching or swelling appears after applying the product.

2) Avoid applying product on the wounded, inflamed skin parts.

3) Cautions for the storage and handing

a)Keep out of children.

b)Avoid direct sun light

c)Avoid applying around eyes

DOSAGE AND ADMINISTRATION

for external use only